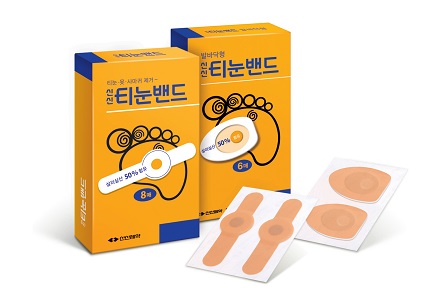 DRUG LABEL: SINSIN CORN BAND
NDC: 72689-0028 | Form: PATCH
Manufacturer: OASIS TRADING
Category: otc | Type: HUMAN OTC DRUG LABEL
Date: 20181213

ACTIVE INGREDIENTS: SALICYLIC ACID 32 mg/1 1
INACTIVE INGREDIENTS: LANOLIN

SINSIN CORN BAND

Active ingredient

Salicylic acid

Purpose

Corn and Callus remover

Warnings

Please refer to the leaflet attached.

Keep out of reach of children.

Directions

The medial part of the drug is attached to cover the affected part and is usually replaced every 2 to 5 days.

Inactive ingredients

lanolin, felt, etc.

INDICATIONS AND USAGE

For external use only